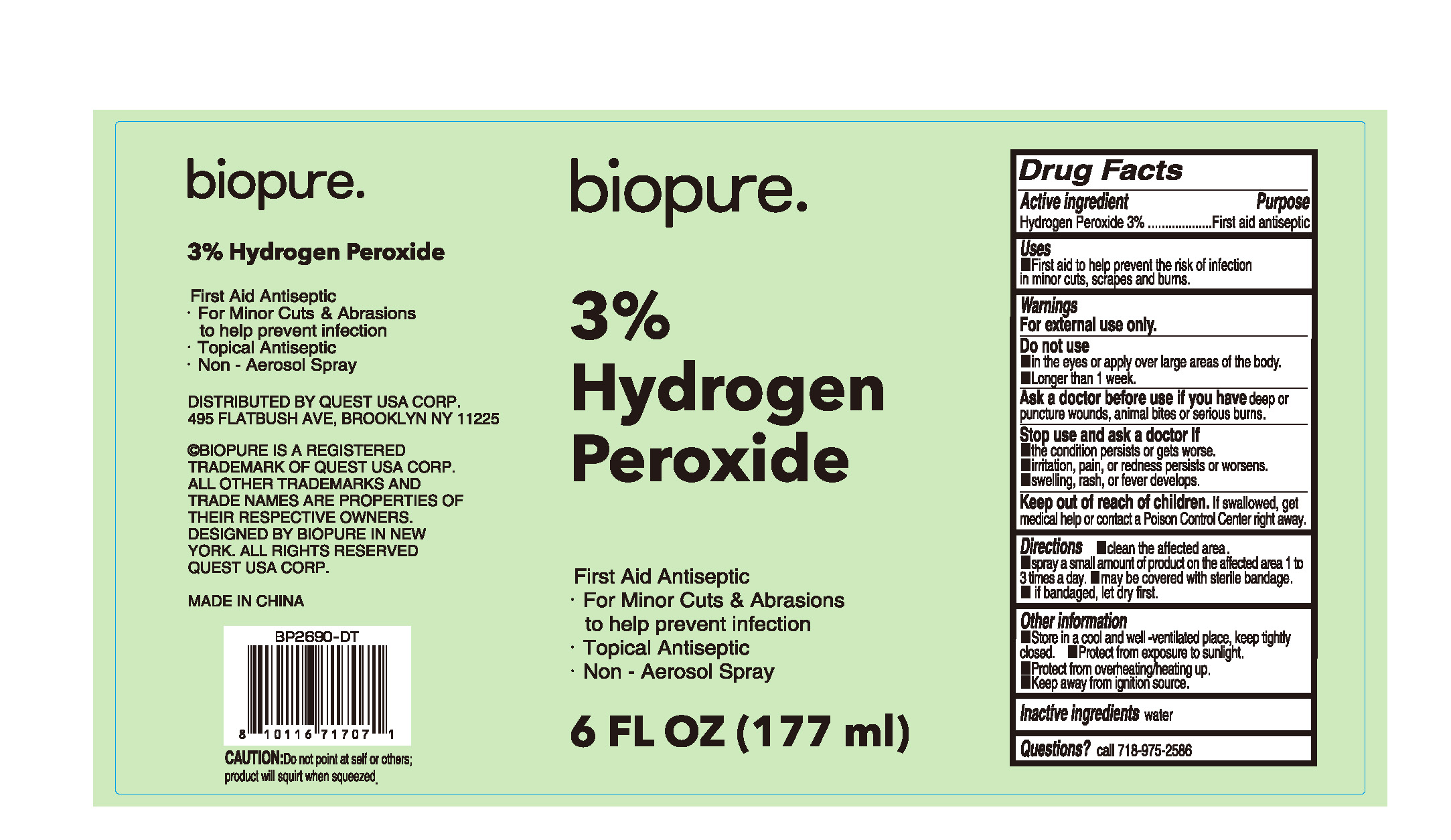 DRUG LABEL: HYDROGEN PEROXIDE
NDC: 79794-111 | Form: LIQUID
Manufacturer: Zhejiang Furuisen Spunlaced Nonwovens Co., Ltd.
Category: otc | Type: HUMAN OTC DRUG LABEL
Date: 20240719

ACTIVE INGREDIENTS: HYDROGEN PEROXIDE 3 g/100 g
INACTIVE INGREDIENTS: WATER

79794-111

Active ingredient

HYDROGEN PEROXIDE 3%

Purpose

First aid antiseptic

Uses

First aid to help prevent hen risk of infection in minor cuts ,scrapes abd burns.

Warnings

For external use only.

Do not use

●in the eyes or apply over large areas of the body.

●Longer than 1 week.

Ask a doctor before use if you have

deep or puncture wounds, animal bites or serious burns

Stop use and ask a doctor

the condition persists or get worse.

irritation,pain, or redness persists or worsens.

swelling, rash, or fever develops.

Keep out of reach of children.

If swallowed. get medical help or contact a Poison Control Center right away.

Directions

Clean the affected area.
Spray a amount of product on the affected area 1 to 3 times a day .
May be covered with sterile bandage.

If bandaged,let dry first.

Other information

●Store in a cool and well-ventilated place, keep tightly closed.

●Protect from exposure to sunlight.

●Protect from overheating/heating up.

●Keep away from ignition source.

Inactive ingredients

Water

Question?

Call 718-975-2586